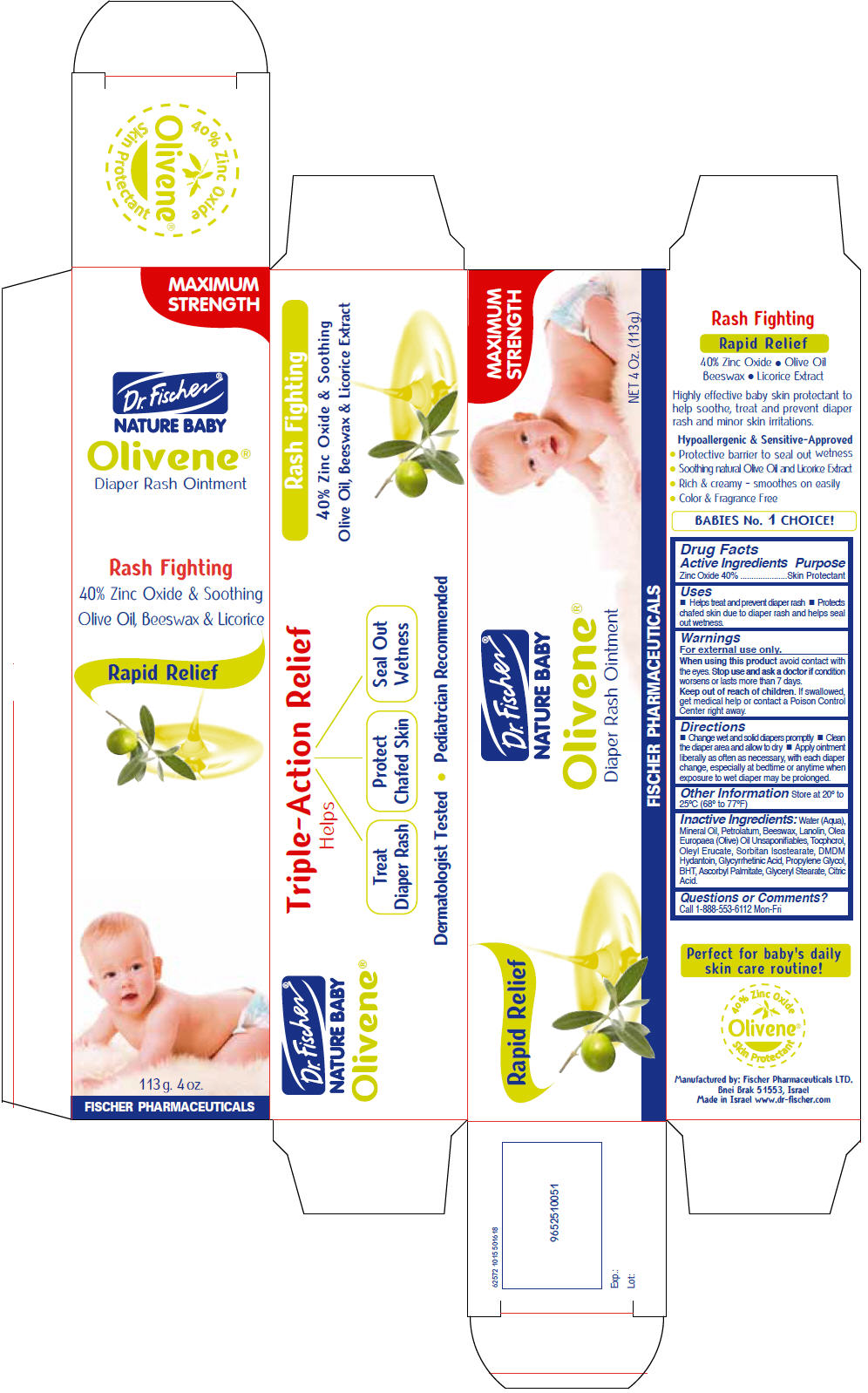 DRUG LABEL: Olivene 
NDC: 59886-413 | Form: OINTMENT
Manufacturer: Fischer Pharmaceuticlas Ltd.
Category: otc | Type: HUMAN OTC DRUG LABEL
Date: 20160609

ACTIVE INGREDIENTS: Zinc Oxide 400 mg/1 g
INACTIVE INGREDIENTS: Water; Mineral Oil; Petrolatum; Yellow Wax; Lanolin; Olive Oil; Oleyl Erucate; Sorbitan Isostearate; DMDM Hydantoin; Enoxolone; Propylene Glycol; Butylated Hydroxytoluene; Ascorbyl Palmitate; Glyceryl Monostearate; Citric Acid Monohydrate

Olivene®
Diaper Rash

Drug Facts

Active Ingredients

Zinc Oxide 40%

Purpose

Skin Protectant

Uses

- Helps treat and prevent diaper rash
- Protects chafed skin due to diaper rash and helps seal out wetness.

Warnings

For external use only.

When using this product avoid contact with the eyes.

Stop use and ask a doctor if condition worsens or lasts more than 7 days.

Keep out of reach of children. If swallowed, get medical help or contact a Poison Control Center right away.

Directions

- Change wet and solid diapers promptly
- Clean the diaper area and allow to dry
- Apply ointment liberally as often as necessary, with each diaper change, especially at bedtime or anytime when exposure to wet diaper may be prolonged.

Other Information

Store at 20° to 25°C (68° to 77°F)

Inactive Ingredients

Water (Aqua), Mineral Oil, Petrolatum, Beeswax, Lanolin, Olea Europaea (Olive) Oil Unsaponifiables, Oleyl Erucate, Sorbitan Isostearate, DMDM Hydantoin, Glycyrrhetinic Acid, Propylene Glycol, BHT, Ascorbyl Palmitate, Glyceryl Stearate, Citric Acid.

Questions or Comments?

Call 1-888-553-6112 Mon-Fri

Manufactured by: Fischer Pharmaceuticals LTD.
Bnei Brak 51553, Israel

PRINCIPAL DISPLAY PANEL - 113 g. Tube Carton

MAXIMUM
STRENGTH

Dr. Fischer®

NATURE BABY

Olivene®
Diaper Rash Ointment

Rash Fighting
40% Zinc Oxide & Soothing
Olive Oil, Beeswax & Licorice

Rapid Relief

113 g. 4 oz.

FISCHER PHARMACEUTICALS